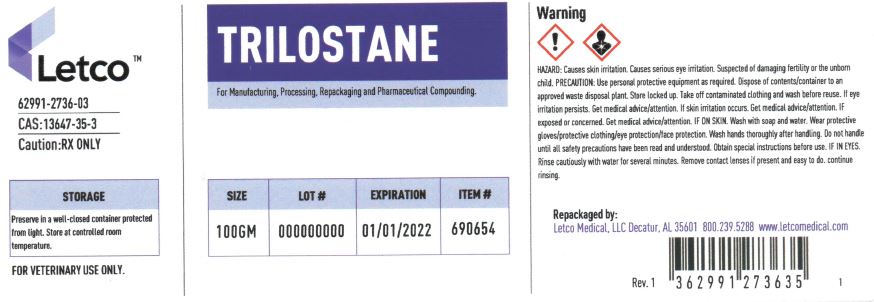 DRUG LABEL: Trilostane
NDC: 62991-2736 | Form: POWDER
Manufacturer: LETCO MEDICAL, LLC
Category: other | Type: BULK INGREDIENT - ANIMAL DRUG
Date: 20240718

ACTIVE INGREDIENTS: TRILOSTANE 1 g/1 g

Trilostane

PACKAGE LABEL

Trilostane 100gm